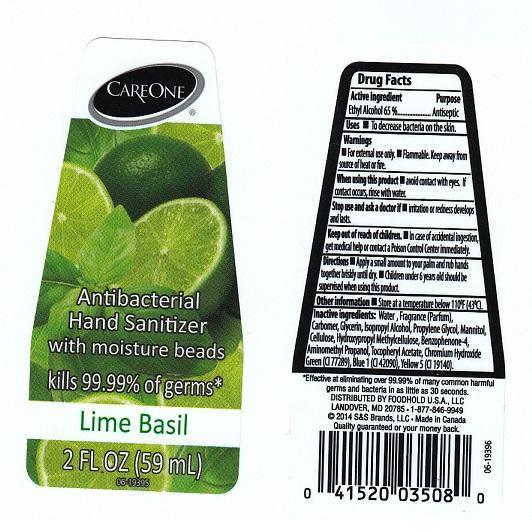 DRUG LABEL: CAREONE
NDC: 41520-423 | Form: LIQUID
Manufacturer: AMERICAN SALES COMPANY
Category: otc | Type: HUMAN OTC DRUG LABEL
Date: 20140221

ACTIVE INGREDIENTS: ALCOHOL 650 mg/1 mL
INACTIVE INGREDIENTS: WATER; CARBOMER 934; GLYCERIN; ISOPROPYL ALCOHOL; PROPYLENE GLYCOL; MANNITOL; POWDERED CELLULOSE; HYPROMELLOSES; SULIBENZONE; AMINOMETHYLPROPANOL; .ALPHA.-TOCOPHEROL ACETATE; CHROMIUM HYDROXIDE GREEN; FD&C BLUE NO. 1; FD&C YELLOW NO. 5

DRUG FACTS

ACTIVE INGREDIENT

ETHYL ALCOHOL 65%

PURPOSE

ANTISEPTIC

USES

TO DECREASE BACTERIA ON THE SKIN

WARNINGS

FOR EXTERNAL USE ONLY. FLAMMABLE. KEEP AWAY FROM SOURCE OF HEAT OR FIRE

WHEN USING THIS PRODUCT

AVOID CONTACT WITH EYES. IF CONTACT OCCURS, RINSE WITH WATER

STOP USE AND ASK A DOCTOR IF

IRRITATION OR REDNESS DEVELOPS AND LASTS

KEEP OUT OF REACH OF CHILDREN

IN CASE OF ACCIDENTAL INGESTION, GET MEDICAL HELP OR CONTACT A POISON CONTROL CENTER IMMEDIATELY

DIRECTIONS

APPLY A SMALL AMOUNT TO YOUR PALM AND RUB HANDS TOGETHER BRISKLY UNTIL DRY. CHILDREN UNDER 6 YEARS OLD SHOULD BE SUPERVISED WHEN USING THIS PRODUCT

OTHER INFORMATION

STORE AT A TEMPERATURE BELOW 110°F (43°C)

INACTIVE INGREDIENTS

WATER, FRAGRANCE (PARFUM), CARBOMER, GLYCERIN, ISOPROPYL ALCOHOL, PROPYLENE GLYCOL, MANNITOL, CELLULOSE, HYDROXYPROPYL METHYLCELLULOSE, BENZOPHENONE-4, AMINOMETHYL PROPANOL, TOCOPHERYL ACETATE, CHROMIUM HYDROXIDE GREEN (CI 77289), BLUE 1 (CI 42090), YELLOW 5 (CI 19140)